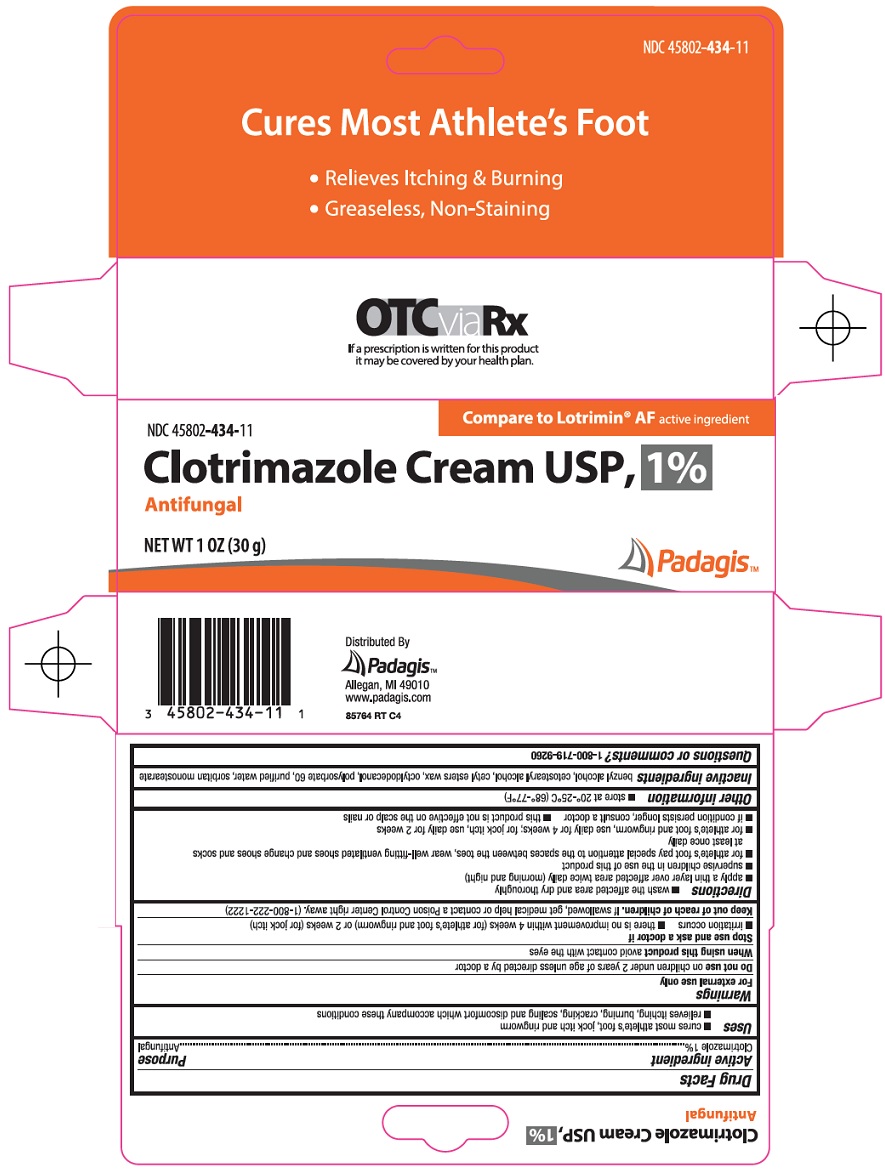 DRUG LABEL: clotrimazole
NDC: 45802-434 | Form: CREAM
Manufacturer: Padagis Israel Pharmaceuticals Ltd
Category: otc | Type: HUMAN OTC DRUG LABEL
Date: 20260122

ACTIVE INGREDIENTS: CLOTRIMAZOLE 1 g/100 g
INACTIVE INGREDIENTS: BENZYL ALCOHOL; CETOSTEARYL ALCOHOL; CETYL ESTERS WAX; OCTYLDODECANOL; POLYSORBATE 60; WATER; SORBITAN MONOSTEARATE

Clotrimazole Cream USP, 1% Drug Facts

Active ingredient

Clotrimazole 1%

Purpose

Antifungal

Uses

- cures most athlete’s foot, jock itch and ringworm
- relieves itching, burning, cracking, scaling and discomfort which accompany these conditions

Warnings

For external use only

Do not use

on children under 2 years of age unless directed by a doctor

When using this product

avoid contact with the eyes

Stop use and ask a doctor if

- irritation occurs
- there is no improvement within 4 weeks (for athlete’s foot and ringworm) or 2 weeks (for jock itch)

Keep out of reach of children.

If swallowed, get medical help or contact a Poison Control Center right away. (1-800-222-1222)

Directions

- wash the affected area and dry thoroughly
- apply a thin layer over affected area twice daily (morning and night)
- supervise children in the use of this product
- for athlete’s foot pay special attention to the spaces between the toes, wear well-fitting ventilated shoes and change shoes and socks at least once daily
- for athlete’s foot and ringworm, use daily for 4 weeks; for jock itch, use daily for 2 weeks
- if condition persists longer, consult a doctor
- this product is not effective on the scalp or nails

Other information

- store at 20°-25°C (68°-77°F)

Inactive ingredients

benzyl alcohol, cetostearyl alcohol, cetyl esters wax, octyldodecanol, polysorbate 60, purified water, sorbitan monostearate

Questions or comments?

1-800-719-9260

Principal Display Panel

Cures Most Athlete’s Foot

• Relieves Itching & Burning

• Greaseless, Non-Staining

Compare to Lotrimin® AF active ingredient

Clotrimazole Cream USP, 1%

Antifungal

NET WT 1 OZ (30 g)

Padagis™